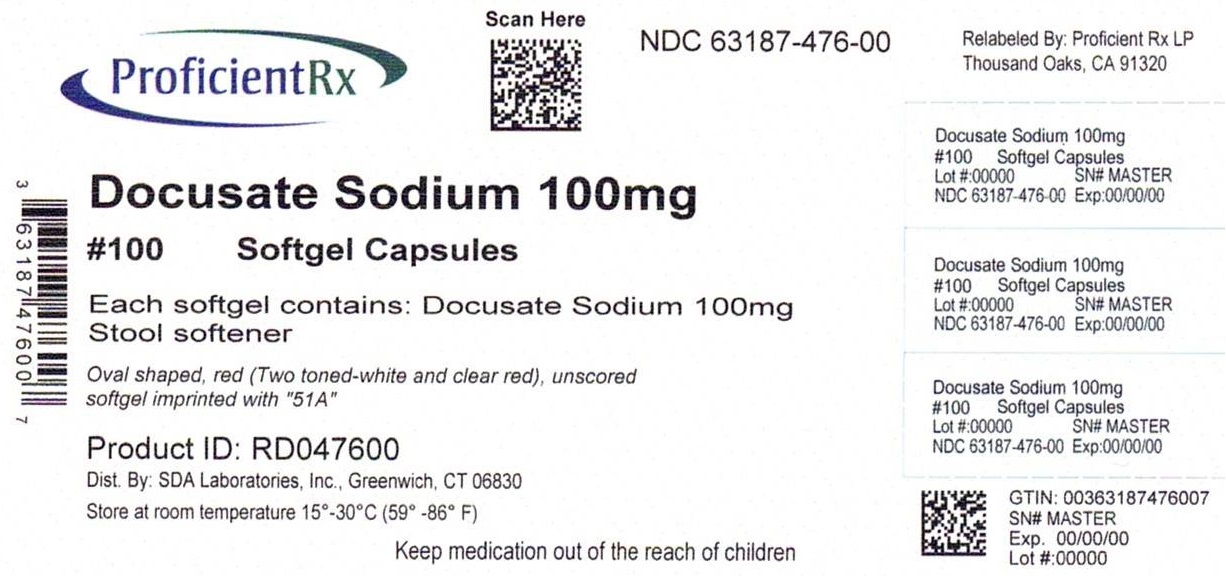 DRUG LABEL: Docusate Sodium
NDC: 63187-476 | Form: CAPSULE, LIQUID FILLED
Manufacturer: Proficient Rx LP
Category: otc | Type: HUMAN OTC DRUG LABEL
Date: 20240201

ACTIVE INGREDIENTS: Docusate Sodium 100 mg/1 1
INACTIVE INGREDIENTS: D&C RED NO. 33; FD&C RED NO. 40; FD&C YELLOW NO. 6; GELATIN, UNSPECIFIED; GLYCERIN; POLYETHYLENE GLYCOL, UNSPECIFIED; PROPYLENE GLYCOL; SORBITOL

Drug Facts

Active ingredient (in each softgel)

Docusate sodium 100 mg

Purpose

Stool softener

Uses

- relieves occasional constipation (irregularity)
- generally produces bowel movement in 12 to 72 hours

Warnings

Do not use

if you are currently taking mineral oil, unless directed by a doctor

Ask a doctor before use if you have

- stomach pain, nausea or vomiting
- have noticed a sudden change in bowel habits that lasts over 2 weeks

Stop use and ask a doctor if

- you have rectal bleeding
- you fail to have a bowel movement after use
- you need to use a stool softener laxative for more than 1 week

If pregnant or breast-feeding,

ask a health professional before use.

Keep out of reach of children.

In case of overdose, get medical help or contact a Poison Control Center right away.

Directions

- doses may be taken as a single daily dose or in divided doses

adults and children 12 years and over | take 1 to 3 softgels daily
children 2 to under 12 years of age | take 1 softgel daily
children under 2 years | ask a doctor

Other information

- each capsule contains sodium 6 mg
- store at room temperature 15o-30oC (59o-86oF)
- Tamper Evident: Do not use if imprinted safety seal under cap is broken or missing

Questions?

Adverse drug event call (800) 687-0176

Principal Display Panel

Relabeled By:

Proficient Rx LP

Thousand Oaks, CA 91320